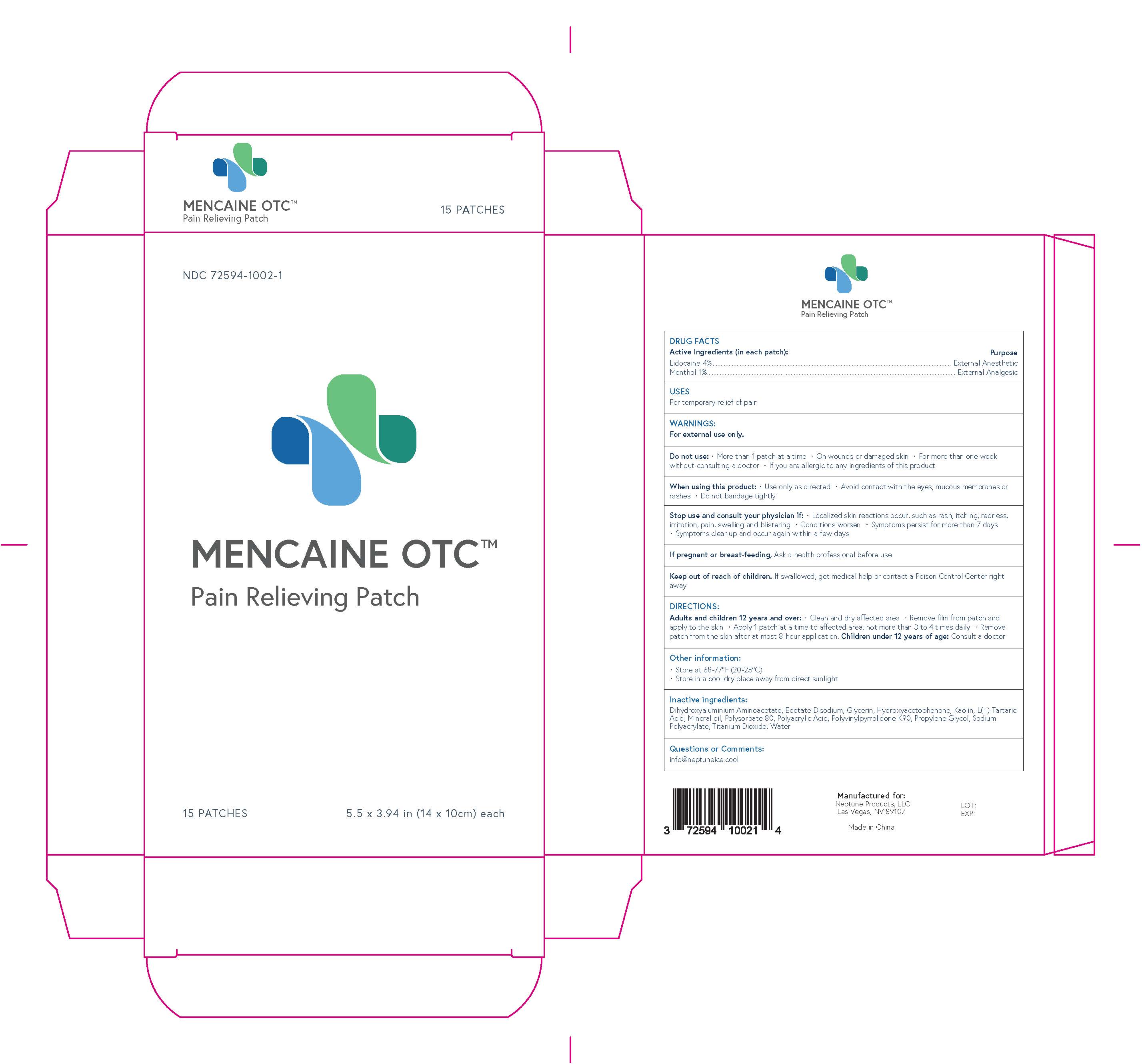 DRUG LABEL: Mencaine OTC
NDC: 72594-1002 | Form: PATCH
Manufacturer: Neptune Products
Category: otc | Type: HUMAN OTC DRUG LABEL
Date: 20241231

ACTIVE INGREDIENTS: LIDOCAINE 4 mg/100 mg; MENTHOL 1 mg/100 mg
INACTIVE INGREDIENTS: HYDROXYACETOPHENONE; MINERAL OIL; POLYACRYLIC ACID (250000 MW); PROPYLENE GLYCOL; TITANIUM DIOXIDE; TARTARIC ACID; WATER; KAOLIN; POLYSORBATE 80; EDETATE DISODIUM; GLYCERIN; DIHYDROXYALUMINUM AMINOACETATE; SODIUM POLYACRYLATE (8000 MW); PVP

Mencaine OTC

Active Ingredients (in each patch):

Lidocaine 4%

Menthol 1%

Purpose

External Anesthetic

External Analgesic

USES

For temporary relief of pain

WARNINGS

For external use only.

Do not use:

• More than 1 patch at a time
• On wounds or damaged skin
• For more than one week without consulting a doctor
• If you are allergic to any ingredients of this product

When using this product:

• Use only as directed
• Avoid contact with the eyes, mucous membranes or rashes
• Do not bandage tightly

Stop use and consult your physician if:

• Localized skin reactions occur, such as rash, itching, redness, irritation, pain, swelling and blistering
• Conditions worsen • Symptoms persist for more than 7 days
• Symptoms clear up and occur again within a few days

If pregnant or breast-feeding,

Ask a health professional before use

Keep out of reach of children.

If swallowed, get medical help or contact a Poison Control Center right away

DIRECTIONS:

Adults and children 12 years and over:
• Clean and dry affected area
• Remove film from patch and apply to the skin
• Apply 1 patch at a time to affected area, not more than 3 to 4 times daily
• Remove patch from the skin after at most 8-hour application.
Children under 12 years of age:
Consult a doctor

Other information:

• Store at 68-77°F (20-25°C)
• Store in a cool dry place away from direct sunlight

Inactive ingredients:

Dihydroxyaluminium Aminoacetate, Edetate Disodium, Glycerin, Hydroxyacetophenone, Kaolin, L(+)-Tartaric Acid, Mineral oil, Polysorbate 80, Polyacrylic Acid, Polyvinylpyrrolidone K90, Propylene Glycol, Sodium Polyacrylate, Titanium Dioxide, Water

Questions or Comments:

info@neptuneice.cool